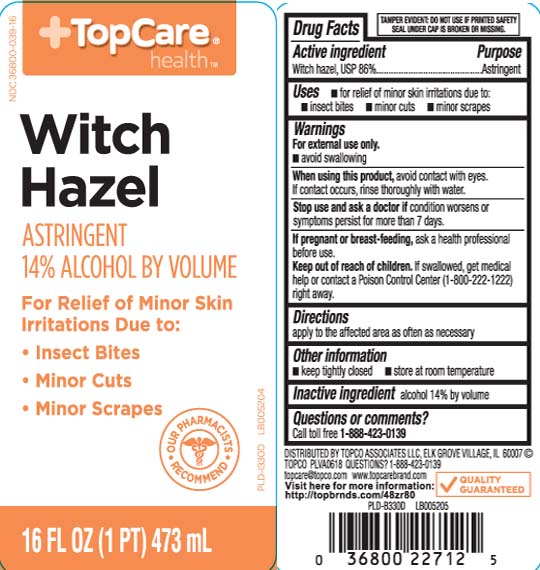 DRUG LABEL: Witch Hazel
NDC: 36800-039 | Form: LIQUID
Manufacturer: TOP CARE (Topco Associates LLC)
Category: otc | Type: HUMAN OTC DRUG LABEL
Date: 20250414

ACTIVE INGREDIENTS: WITCH HAZEL 842 mg/1 mL
INACTIVE INGREDIENTS: ALCOHOL

Drug Facts

Active ingredient

Witch hazel 86%

Purpose

Astringent

Uses

for relief of minor skin irritations due to:

- insect bites
- minor cuts
- minor scrapes

Warnings

- for external use only
- avoid swallowing

When using this product

- avoid contact with the eyes. if contact occurs, rinse thoroughly with water.

Stop use and ask a doctor if

condition worsens or symptoms persist for more than 7 days.

If pregnant or breast-feeding,

ask a health professional before use.

Keep out of reach of children.

If swallowed, get medical help or contact a Poison Control Center (1-800-222-1222) right away..

Directions

apply to the affected area as often as necessary.

Other information

- keep tightly closed
- store at room temperature

Inactive ingredient

alcohol 14% by volume

Questions or comments?

Call toll free 1-888-423-0139

Principal Display Panel

Witch Hazel

ASTRINGENT

14% ALCOHOL BY VOLUME

For relief of minor skin irritations due to:

- Insect bites
- Minor cuts
- MInor scrapes

FL OZ (mL)

TAMPER EVIDENT: DO NOT USE IF PRINTED SAFETY SEAL UNDER CAP IS BROKEN OR MISSING.

DISTRIBUTED BY TOPCO ASSOCIATES LLC

ELK GROVE VILLAGE, IL 60007

topcare@topco.com

Package Label

TOPCARE HEALTH Witch Hazel